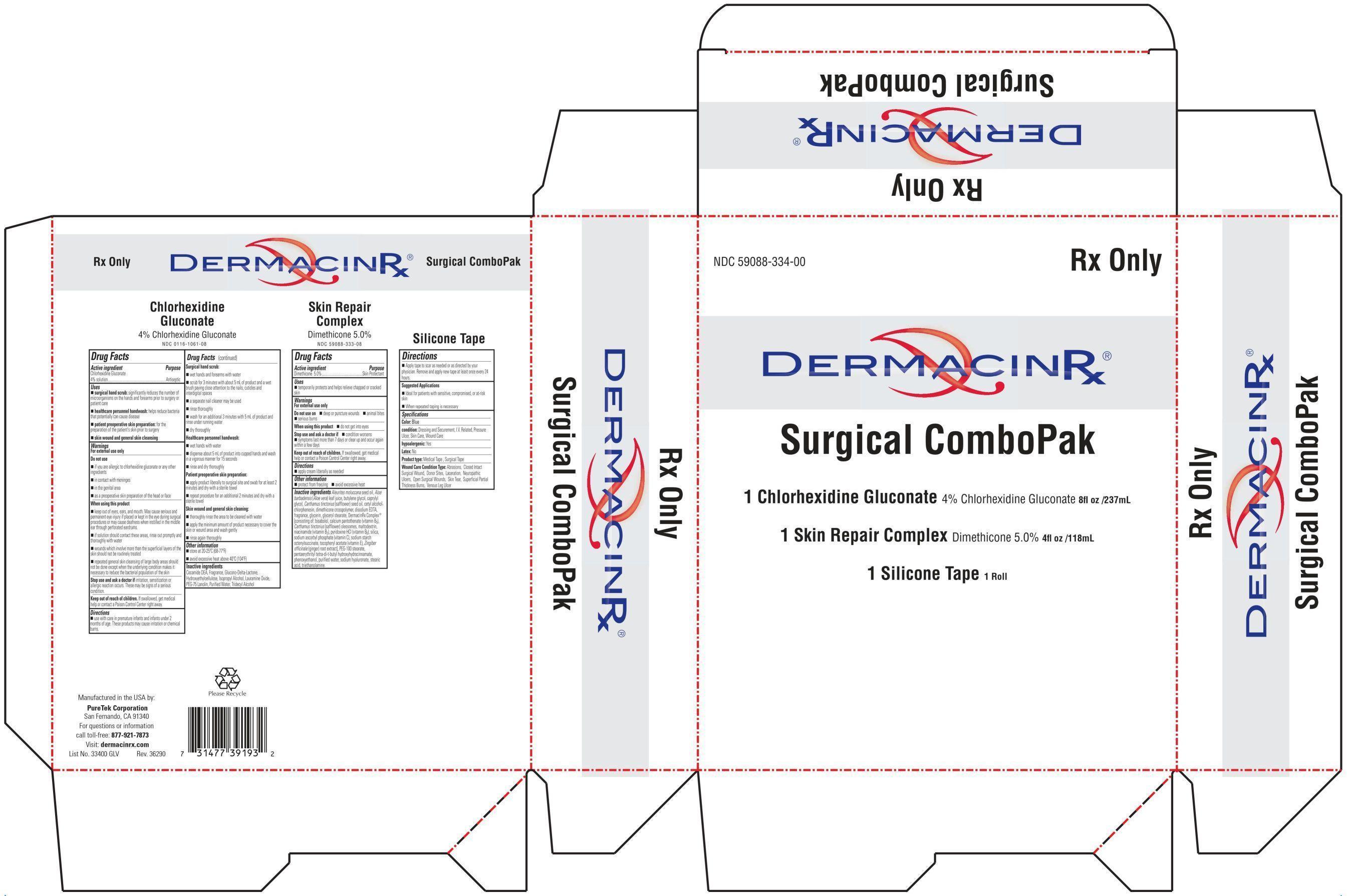 DRUG LABEL: DermacinRx Surgical ComboPak
NDC: 59088-334 | Form: KIT | Route: TOPICAL
Manufacturer: PureTek Corporation
Category: prescription | Type: HUMAN PRESCRIPTION DRUG LABEL
Date: 20241213

ACTIVE INGREDIENTS: CHLORHEXIDINE GLUCONATE 4 g/100 mL; DIMETHICONE 50 mg/1 mL
INACTIVE INGREDIENTS: COCO DIETHANOLAMIDE; HYDROXYETHYL CELLULOSE (2000 CPS AT 1%); ISOPROPYL ALCOHOL; LAURAMINE OXIDE; WATER; TRIDECYL ALCOHOL; GLUCONOLACTONE; PEG-75 LANOLIN; KUKUI NUT OIL; ALOE VERA LEAF; BUTYLENE GLYCOL; CAPRYLYL GLYCOL; SAFFLOWER OIL; CETYL ALCOHOL; CHLORPHENESIN; DIMETHICONE/DIENE DIMETHICONE CROSSPOLYMER; EDETATE DISODIUM; GLYCERIN; GLYCERYL MONOSTEARATE; LEVOMENOL; CALCIUM PANTOTHENATE; CARTHAMUS TINCTORIUS SEED OLEOSOMES; MALTODEXTRIN; NIACINAMIDE; PYRIDOXINE HYDROCHLORIDE; SILICON DIOXIDE; SODIUM ASCORBYL PHOSPHATE; .ALPHA.-TOCOPHEROL ACETATE, DL-; GINGER; PEG-100 STEARATE; PENTAERYTHRITOL TETRAKIS(3-(3,5-DI-TERT-BUTYL-4-HYDROXYPHENYL)PROPIONATE); PHENOXYETHANOL; WATER; HYALURONATE SODIUM; STEARIC ACID; TROLAMINE

DermacinRx Surgical ComboPak

PART 1: Chlorhexidine Gluconate

Drug Facts

Active ingredient

Chlorhexidine Gluconate 4% solution

Purpose

Antiseptic

Uses

- surgical hand scrub: significantly reduces the number of microorganisms on the hands and forearms prior to surgery or patient care
- healthcare personnel handwash: helps reduce bacteria that potentially can cause disease
- patient preoperative skin preparation: for the preparation of the patient's skin prior to surgeryskin wound and general skin cleansing
- skin wound and general skin cleansing

Warnings

For external use only

Do not use

- if you are allergic to chlorhexidine gluconate or any other ingredients
- in contact with meninges
- in the genital area
- as a preoperative skin preparation of the head or face

When using this product

- keep out of eyes, ears, and mouth. May cause serious and permanent eye injury if placed or kept in the eye during surgical procedures or may cause deafness when instilled in the middle ear through perforated eardrums.
- if solution should contact these areas, rinse out promptly and thoroughly with water
- wounds which involve more than the superficial layers of the skin should not be routinely treated
- repeated general skin cleansing of large body areas should not be done except when the underlying condition makes it necessary to reduce the bacterial population of skin

Stop use and ask a doctorif irritation, sensitization or allergic reaction occurs. These may be signs of a serious condition.

Keep out of reach of children.If swallowed, get medical help or contact a Poison Control Center right away.

Directions

use with care in premature infants and infants under 2 months of age. These products may cause irritation or chemical burns.

- Surgical hand scrub:
  - wet hands and forearms with water
  - scrub for 3 minutes with about 5 ml of product and a wet brush paying close attention to the nails, cuticles and interdigital spaces
  - a separate nail cleaner may be used
  - rinse thoroughly
  - wash for an additional 3 minutes with 5 ml of product and rinse under running water
  - dry thoroughly
- Healthcare personnel handwash:
  - wet hands with water
  - dispense about 5 ml of product into cupped hands and wash in a vigorous manner for 15 seconds
  - rinse and dry thoroughly
- Patient preoperative skin preparation:
  - apply product liberally to surgical site and swab for at least 2 minutes and dry with a sterile towel
  - repeat procedure for an additional 2 minutes and dry with a sterile towel
- Skin wound and general skin cleaning:
  - thoroughly rinse the area to be cleaned with water
  - apply the minimum amount of product necessary to cover the skin or wound area and wash gently
  - rinse again thoroughly

Other information

- store at 20-25ºC (68-77ºF)
- avoid excessive heat above 40ºC (104ºF)

Inactive ingredients

cocamide DEA, fragrance, glucono-delta-lactone, hydroxyethylcellulose, isopropyl alcohol, lauramine oxide, PEG-75 lanolin, purified water, tridecyl alcohol

PART 2: Skin Repair Complex

Drug Facts

Active ingredient

Dimethicone 5.0%

Uses

■ for the treatment and/or prevention of diaper rash
■ temporarily protects and helps relieve chapped or cracked skin

Warnings

For external use only

Do not use on ■ deep or puncture wounds ■ animal bites ■ serious burns

When using this product ■ do not get into eyes

Stop use and ask a doctor if■ condition worsens
■ symptoms last more than 7 days or clear up and occur again within a few days

Keep out of reach of children.If swallowed, get medical help or contact a Poison Control Center right away.

Directions

■ apply cream liberally as needed

Other information

■ protect from freezing ■ avoid excessive heat

Inactive ingredients

Aleurites moluccana seed oil, Aloe barbadensis (Aloe vera) leaf juice, butylene glycol, caprylyl glycol, Carthamus tinctorius (safflower) seed oil, cetyl alcohol, chlorphenesin, dimethicone crosspolymer, disodium EDTA, fragrance, glycerin, glyceryl stearate, DermacinRx Complex® [consisting of: bisabolol, calcium pantothenate (vitamin B5), Carthamus tinctorius (safflower) oleosomes, maltodextrin, niacinamide (vitamin B3), pyridoxine HCl (vitamin B6), silica, sodium ascorbyl phosphate (vitamin C), sodium starch octenylsuccinate, tocopheryl acetate (vitamin E), Zingiber officinale (ginger) root extract], PEG-100 stearate, pentaerythrityl tetra-di-t-butyl hydroxyhydrocinnamate, phenoxyethanol, purified water, sodium hyaluronate, stearic acid, triethanolamine.

PART 3: Silicone Tape

Uses
• To be applied to wounds or scars as a protective silicone barrier.
• As a dressing for abrasions, surgical wounds, donor sites, lacerations, ulcers, skin tears, superficial partial thickness burns, venous leg ulcers.
• As a dressing/securement for IV related uses, pressure ulcers, skin care, and wound care

Precautions
• Do not use if you are allergic to silicone
• Keep out of reach of children

Directions for use
• Apply tape to wound or scar as needed or as directed by your physician. Remove tape, wash area, and apply new tape at least every 24 hours.